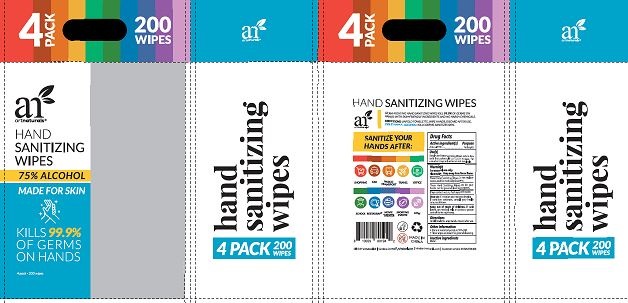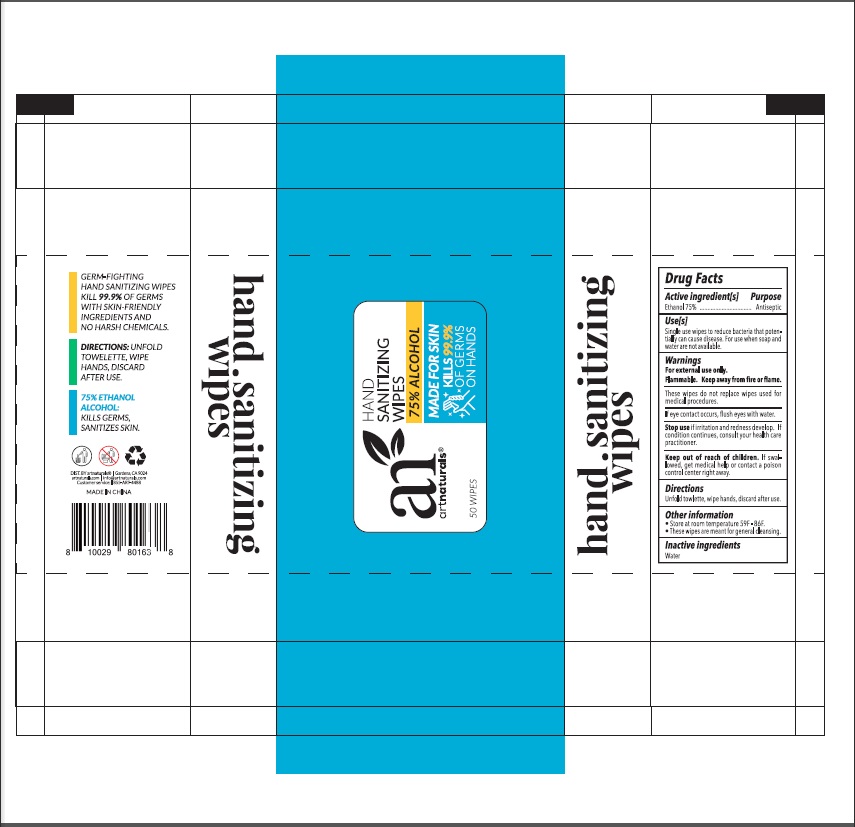 DRUG LABEL: All Around Sanitizing Wipes
NDC: 79650-200 | Form: LIQUID
Manufacturer: Zhangzhou Zhongnan Nursing Products Co., Ltd.
Category: otc | Type: HUMAN OTC DRUG LABEL
Date: 20201123

ACTIVE INGREDIENTS: ALCOHOL 75 mL/100 mL
INACTIVE INGREDIENTS: WATER

Active ingredient[s]

Ethanol 75%

Purpose

Antiseptic

Use[s]

Single use wipes to reduce bacterial that potentially can cause disease. For use when soap and water are not available.

Warnings

For external use only. Flammable, Keep away from fire or flame.

These wipes do not replace wipes used for medical procedures.

If eye contact occurs, flush eyes with water.

Stop use

Stop use If irritation and redness develop. If condition continues, consult your health care practitioner.

Keep out of reach of children. If swallowed, get medical help or contact a Poison Control Center right away.

Directions

Unfold towlette, wipe hands, discard after use.

Inactive ingredients

Water